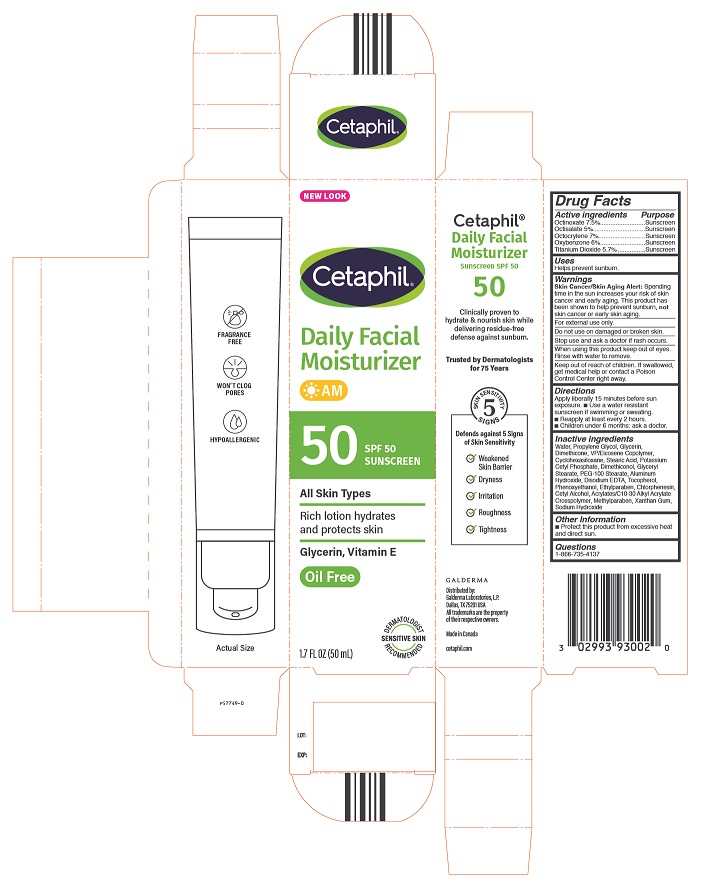 DRUG LABEL: Cetaphil Daily Facial Moisturizer with suncreen SPF 50
NDC: 0299-4930 | Form: LOTION
Manufacturer: Galderma Laboratories, L.P.
Category: otc | Type: HUMAN OTC DRUG LABEL
Date: 20240417

ACTIVE INGREDIENTS: OCTINOXATE 75 mg/1 mL; OCTISALATE 50 mg/1 mL; OCTOCRYLENE 70 mg/1 mL; OXYBENZONE 60 mg/1 mL; TITANIUM DIOXIDE 57 mg/1 mL
INACTIVE INGREDIENTS: WATER; PROPYLENE GLYCOL; GLYCERIN; DIMETHICONE; VINYLPYRROLIDONE/EICOSENE COPOLYMER; Cyclomethicone 6; STEARIC ACID; Potassium Cetyl Phosphate; Dimethiconol (40 Cst); GLYCERYL MONOSTEARATE; PEG-100 STEARATE; ALUMINUM HYDROXIDE; EDETATE DISODIUM; TOCOPHEROL; Phenoxyethanol; Ethylparaben; Chlorphenesin; Cetyl Alcohol; Acrylates/C10-30 Alkyl Acrylate Crosspolymer (60000 Mpa.S); Methylparaben; Xanthan Gum; Sodium Hydroxide

Cetaphil Daily Facial Moisturizer with suncreen SPF 50+

Active Ingredients

Octinoxate 7.5%
Octisalate 5%
Octocrylene 7%
Oxybenzone 6%
Titanium Dioxide 5.7%

Purpose

Sunscreen

Uses

Helps prevent sunburn.

Warnings

Skin Cancer/Skin Aging Alert:

Spending time in the sun increases your risk of skin cancer and early aging. This product has been shown to help prevent sunburn, not skin cancer or early aging.

For external use only.

Do not use on damaged or broken skin.

Stop use and ask a doctor if rash occurs.

When using this product keep out of eyes. Rinse with water to remove.

Keep out of reach of children. If swallowed, get medical help or contact a Poison Control Center right away.

Directions

Apply liberally 15 minutes before sun exposure. • Use a water resistant sunscreen if swimming or sweating. • Reapply at least every 2 hours. • Children under 6 months: ask a doctor.

Inactive Ingredients

Water, Propylene Glycol, Glycerin, Dimethicone, VP/Eicosene Copolymer ,Cyclohexasiloxane, Stearic Acid, Potassium Cetyl Phosphate, Dimethiconol, Glyceryl Stearate, PEG-100 Stearate, Aluminum Hydroxide, Disodium EDTA, Tocopherol, Phenoxyethanol, Ethylparaben, Chlorphenesin, Cetyl Alcohol, Acrylates/C10-30 Alkyl Acrylate, Crosspolymer, Methylparaben, Xanthan Gum, Sodium Hydroxide

Other Information

• Protect this product from excessive heat and direct sun.

Questions?

1-866-735-4137

Principal Display Panel - 1.7oz carton

NEW LOOK

Cetaphil®
Daily Facial
Moisturizer
AM

50 SPF 50
Sunscreen

All Skin Types

Rich lotion hydrates
and protects skin

Glycerin, Vitamin E

Oil Free
Dermatologist Recommended
Sensitive Skin
1.7 FL OZ (50 mL)

Distributed by:

Galderma Laboratories, L.P.

Dallas, TX 75201 USA

All trademarks are the property of their respective owners.

Made in Canada

cetaphil.com
P57749-0